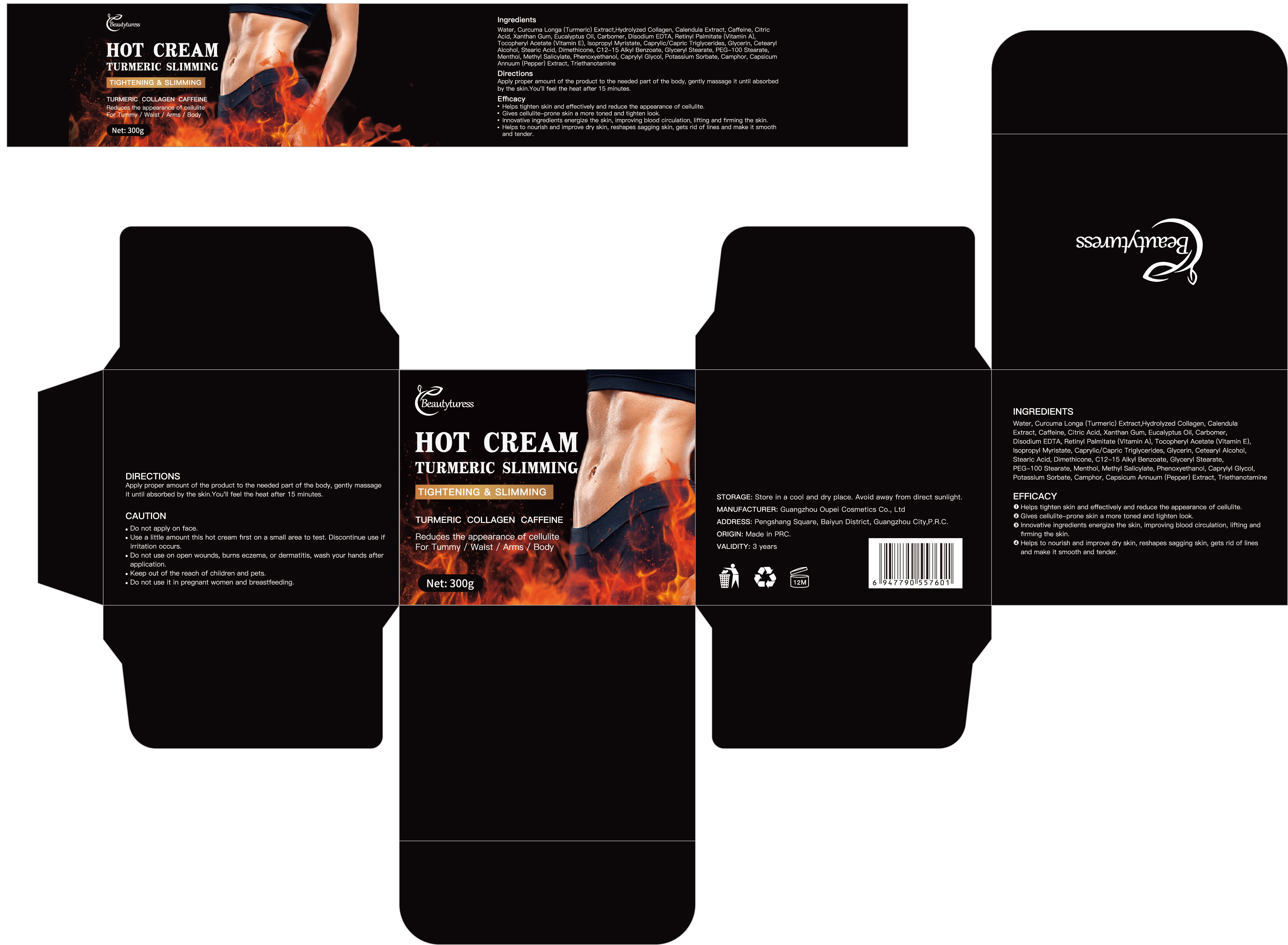 DRUG LABEL: Beautyturess Slimming Lifting Firming Cream
NDC: 84753-002 | Form: EMULSION
Manufacturer: Guangdong Bisutang Biotechnology Co., Ltd.
Category: otc | Type: HUMAN OTC DRUG LABEL
Date: 20241007

ACTIVE INGREDIENTS: LEVOCARNITINE 30 mg/300 g; CAPSICUM ANNUUM VAR. ANNUUM HOT CULTIVAR GROUP WHOLE 60 mg/300 g
INACTIVE INGREDIENTS: PEG-9 DIGLYCIDYL ETHER/SODIUM HYALURONATE CROSSPOLYMER; ISOHEXADECANE; CETYL HYDROXYETHYLCELLULOSE (550000 MW); WATER; FRAGRANCE 13576; POLYSORBATE 80; METHYLPARABEN; DISODIUM EDTA-COPPER; 1,3-BUTYLENE GLYCOL 1-PROPIONATE; PEG-6 SORBITAN OLEATE; FOLIC ACID

ACTIVE INGREDIENT

Capsicum Annuum Extract 60mg

Carnitine 30mg

PURPOSE

This product promotes local blood circulation and assists in fat metabolism through gentle heating, helping to lift and firm the skin.

Ask Doctor

If you have a history of skin allergies or have sensitive skin, it is advisable to consult a doctor before using this product.

DOSAGE AND ADMINISTRATION

Apply an appropriate amount of the product evenly to the areas that need lifting and firming, and gently massage until fully absorbed. It is recommended to use 1-2 times daily for best results.

WHEN USING

Avoid contact with eyes and broken skin. If redness, swelling, or irritation occurs, discontinue use immediately and seek medical advice.

WARNINGS

Risk InformationFor external use only
Mention de risquesPour usage externe seulement
Do not use on damaged or broken skin.
Ne pas utiliser sur la peau endommagée ou avec des lésions
If rash occurs, discontinue use and consult a health care practitioner.
En présence d'une éruption cutanée, cesser l'utilisation et consulter un praticien de soins de santé
When using this product keep out of eyes. Rinse with water to remove.
Eviter tout contact avec les yeux. Rincer a l'eau le cas échéant
Keep out of reach of children. If swallowed, get medical help or contact a Poison Control Center right away.
Tenir hors de portée des enfants
En cas d'ingestion, consulter un médecin ou appeler un centre antipoison immédiatement.

INDICATIONS AND USAGE

This product is designed to help lift and firm the skin, supporting local slimming effects for a tighter and smoother appearance.

Keep out of reach of children. If swallowed, get medical help or contact a Poison Control Center right away.
Tenir hors de portée des enfants
En cas d'ingestion, consulter un médecin ou appeler un centre antipoison immédiatement.

INACTIVE INGREDIENT

（AQUA）
（ISOHEXADECANE）
（POLYSORBATE 80）
（SORBITAN OLEATE）
（METHYLPARABEN）
（DISODIUM EDTA）
（HYDROXYETHYLCELLULOSE）
（FRAGRANCE）
（AQUA）
（BUTYLENE GLYCOL）
（1,2-HEXANEDIOL）
（BACILLUS/SOYBEAN FERMENT EXTRACT）
（FOLIC ACID）
（SODIUM HYALURONATE）